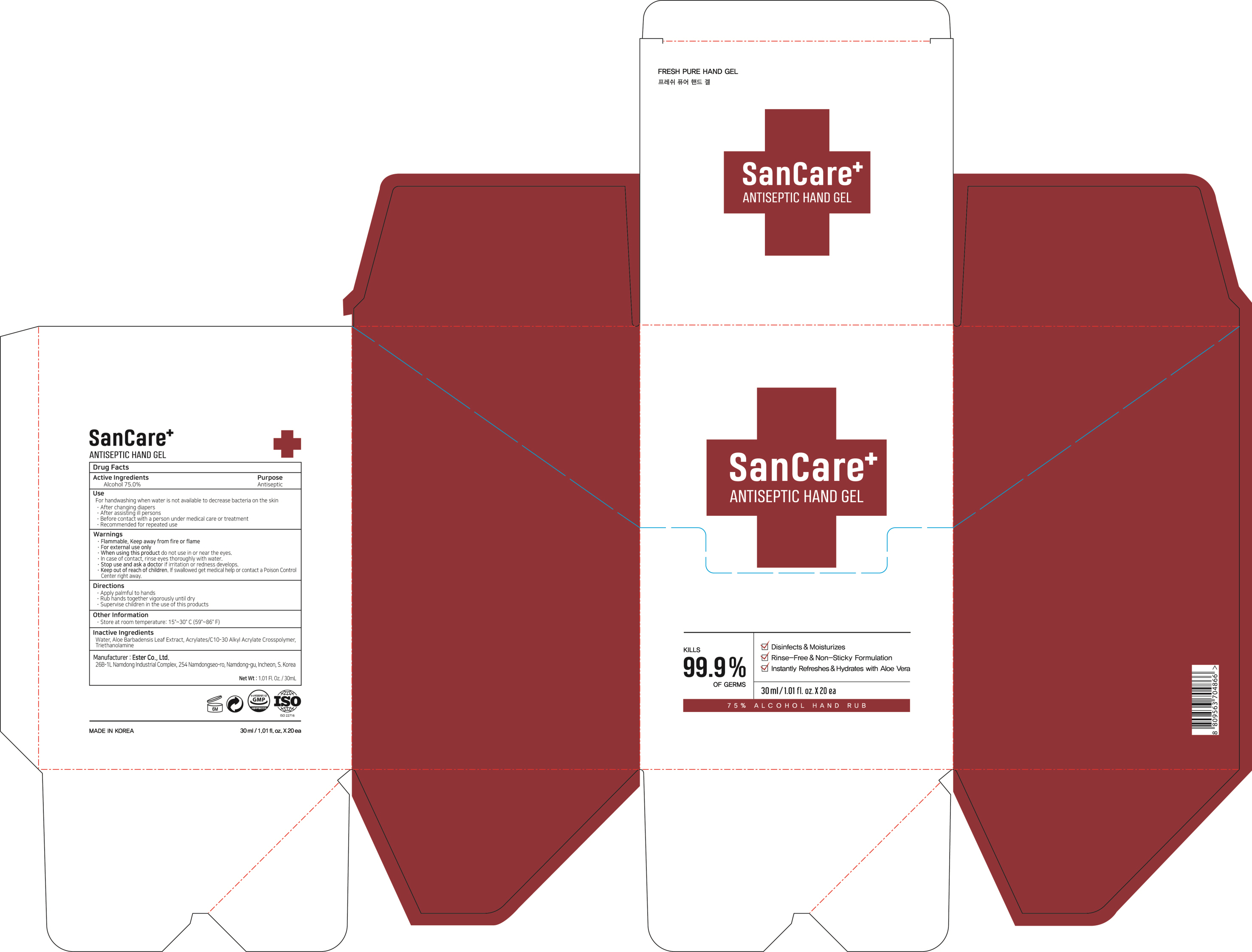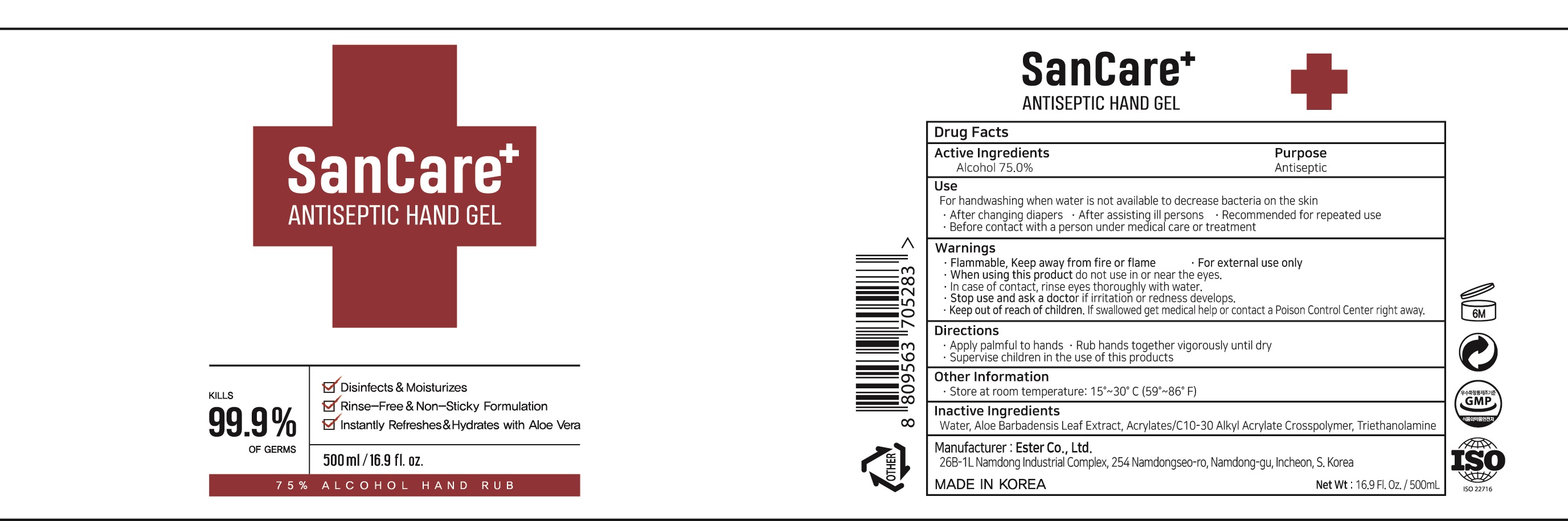 DRUG LABEL: Sancare Antiseptic Hand
NDC: 74004-010 | Form: GEL
Manufacturer: Ester Co., Ltd.
Category: otc | Type: HUMAN OTC DRUG LABEL
Date: 20201111

ACTIVE INGREDIENTS: ALCOHOL 75 g/100 mL
INACTIVE INGREDIENTS: WATER; ALOE VERA LEAF; CARBOMER INTERPOLYMER TYPE A (ALLYL SUCROSE CROSSLINKED); TROLAMINE

74004-010 Sancare Antiseptic Hand

ACTIVE INGREDIENT

Active ingredients: ALCOHOL 75%

INACTIVE INGREDIENT

Inactive ingredients:

Water, Aloe Barbadensis Leaf Extract, Acrylates/C10-30 Alkyl Acrylate Crosspolymer, Triethanolamine

PURPOSE

Purpose: ANTISEPTIC

WARNINGS

Flammable, Keep away from fire or flame
For external use only

When using this product do not use in or near the eyes.
In case of contact, rinse eyes thoroughly with water.

Stop use and ask a doctor if irritation or redness develops.

Keep our of reach of children. If swallowed get medical help or contact a Poison Control Center right away.

KEEP OUT OF REACH OF CHILDREN

Keep our of reach of children. If swallowed get medical help or contact a Poison Control Center right away.

Uses

For handwashing when water is not available to decrease bacteria on the skin
- after changing diapers
- after assisting ill persons
- before contact with a person under medical care or treatment
- recommended for repeated use

Directions

- apply palmful to hands
- rub hands together vigorously until dry
- supervise children in the use of this product